DRUG LABEL: Ear Wax Removal Aid
NDC: 49794-003 | Form: LIQUID
Manufacturer: Continental Manufacturing Chemist, Inc.
Category: otc | Type: HUMAN OTC DRUG LABEL
Date: 20110317

ACTIVE INGREDIENTS: carbamide peroxide 6.5 mg/100 mL
INACTIVE INGREDIENTS: glycerin

DOSAGE AND ADMINISTRATION

DIRECTIONS: For use in the ear only. For use by adults and children over 12 years of age. Tilt head sideways and place 5 to 10 drops into ear. Tip of applicator should not enter ear canal. Keep drops in ear for several minutes by keeping head tilted, or placing cotton in ear. Use twice daily for up to 4 days, if needed or as directed by a physician. Any wax remaining after treatment may be removed by gently flushing the ear with warm water, using a soft rubber bulb ear syringe. For children under 12 years of age, consult a physician. NOTE: When the ear canal is irrigated, the tip of the ear syringe should not obstruct the flow of water leaving the ear canal.

WARNINGS

WARNINGS: DO NOT USE if you have ear drainage or discharge, ear pain, irritation, or rash in the ear, or if you are dizzy; consult a physician. DO NOT USE if you have an injury or perforation (hole) of the eardrum or after ear surgery, unless directed by a physician. DO NOT USE for more than 4 days; if excessive earwax remains after use of this product, consult a physician. Avoid contact with eyes. If swallowed, get medical help or contact a Poison Control Center right away.

ACTIVE INGREDIENT: Carbamide Peroxide 6.5%

KEEP OUT OF REACH OF CHILDREN

PURPOSE

Softens and removes excessive earwax safely and gently.

Inactive Ingredient: anhydrous glycerin

INDICATIONS AND USAGE

Uses for occasional use as an aid to soften, loosen and remove excessive earwax.